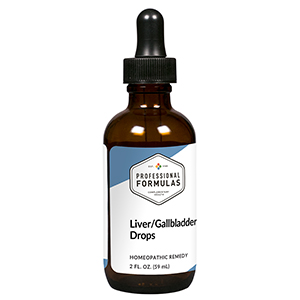 DRUG LABEL: Liver/Gallbladder Drops
NDC: 63083-5012 | Form: LIQUID
Manufacturer: Professional Complementary Health Formulas
Category: homeopathic | Type: HUMAN OTC DRUG LABEL
Date: 20190815

ACTIVE INGREDIENTS: MILK THISTLE 2 [hp_X]/59 mL; BEEF LIVER 6 [hp_X]/59 mL; BOS TAURUS GALLBLADDER 6 [hp_X]/59 mL; CHELIDONIUM MAJUS WHOLE 6 [hp_X]/59 mL; LYCOPODIUM CLAVATUM SPORE 6 [hp_X]/59 mL; STRYCHNOS NUX-VOMICA SEED 6 [hp_X]/59 mL
INACTIVE INGREDIENTS: ALCOHOL; WATER

HLGD

ACTIVE INGREDIENTS

Carduus marianus 2X
Liver 6X, 12X, 30X, 60X, 100X
Gallbladder 6X, 12X, 30X, 60X, 100X
Chelidonium majus 6X
Lycopodium clavatum 6X
Nux vomica 6X

QUESTIONS

Professional Formulas

PO Box 2034 Lake Oswego, OR 97035

INDICATIONS

For the temporary relief of minor abdominal pain or swelling, fatigue, irritability, constipation, loss of appetite, or low energy level.*

PURPOSE

*Claims based on traditional homeopathic practice, not accepted medical evidence. Not FDA evaluated.

WARNINGS

Severe or persistent symptoms may be serious. Consult a doctor promptly. Keep out of the reach of children. In case of overdose, get medical help or contact a poison control center right away. If pregnant or breastfeeding, ask a healthcare professional before use.

Keep out of the reach of children.

PREGNANCY OR BREAST FEEDING

If pregnant or breastfeeding, ask a healthcare professional before use.

DIRECTIONS

Place drops under tongue 30 minutes before/after meals. Adults and children 12 years and over: Take 10 drops up to 3 times per day. Consult a physician for use in children under 12 years of age.

OTHER INFORMATION

Tamper resistant. If seal is broken, do not use. After opening, close container tightly and store at room temperature away from heat.

INACTIVE INGREDIENTS

20% ethanol, purified water.

LABEL

Est 1985

Professional Formulas

Complementary Health

Liver/Gallbladder Drops

Homeopathic Remedy

2 FL. OZ. (59 mL)